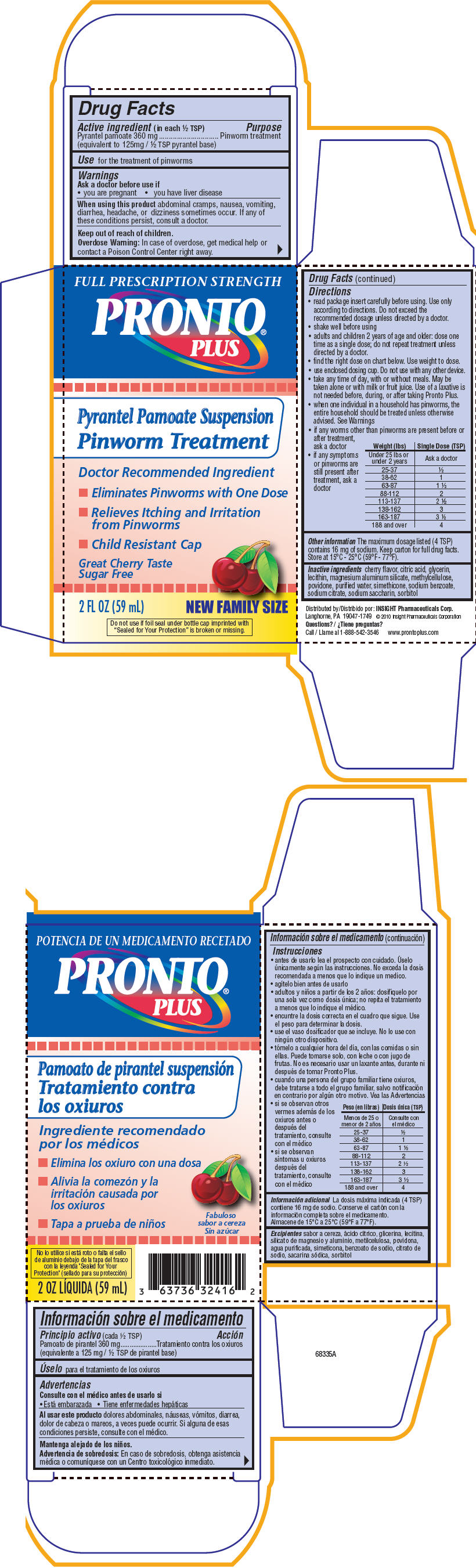 DRUG LABEL: Pronto Plus 
NDC: 63736-240 | Form: LIQUID
Manufacturer: Insight Pharmaceuticals LLC
Category: otc | Type: HUMAN OTC DRUG LABEL
Date: 20101110

ACTIVE INGREDIENTS: Pyrantel pamoate 5 mL/250 mL
INACTIVE INGREDIENTS: Citric Acid Monohydrate; Glycerin; magnesium aluminum silicate; povidone; water; sodium benzoate; sodium citrate; saccharin sodium; sorbitol; cyclomethicone 6

PRONTO®
PLUS
Pyrantel Pamoate Suspension
Pinworm Treatment

Drug Facts

Active ingredient (in each ½ TSP)

Pyrantel pamoate 360 mg

(equivalent to 125mg / ½ TSP pyrantel base)

Purpose

Pinworm treatment

Use

for the treatment of pinworms

Warnings

Ask a doctor before use if

- you are pregnant
- you have liver disease

When using this product abdominal cramps, nausea, vomiting, diarrhea, headache, or dizziness sometimes occur. If any of these conditions persist, consult a doctor.

Keep out of reach of children.

Overdose Warning

In case of overdose, get medical help or contact a Poison Control Center right away.

Directions

- read package insert carefully before using. Use only according to directions. Do not exceed the recommended dosage unless directed by a doctor.
- shake well before using
- adults and children 2 years of age and older: dose one time as a single dose; do not repeat treatment unless directed by a doctor.
- find the right dose on chart below. Use weight to dose.
- use enclosed dosing cup. Do not use with any other device.
- take any time of day, with or without meals. May be taken alone or with milk or fruit juice. Use of a laxative is not needed before, during, or after taking Pronto Plus.
- when one individual in a household has pinworms, the entire household should be treated unless otherwise advised. See Warnings
- if any worms other than pinworms are present before or after treatment, ask a doctor
- if any symptoms or pinworms are still present after treatment, ask a doctor

Weight (lbs) | Single Dose (TSP)
Under 25 lbs or under 2 years | Ask a doctor
25-37 | ½
38-62 | 1
63-87 | 1 ½
88-112 | 2
113-137 | 2 ½
138-162 | 3
163-187 | 3 ½
188 and over | 4

Other information

The maximum dosage listed (4 TSP) contains 16 mg of sodium. Keep carton for full drug facts. Store at 15°C - 25°C (59°F - 77°F).

Inactive ingredients

cherry flavor, citric acid, glycerin, lecithin, magnesium aluminum silicate, methylcellulose, povidone, purified water, simethicone, sodium benzoate, sodium citrate, sodium saccharin, sorbitol

Distributed by: INSIGHT Pharmaceuticals Corp.
Langhorne, PA 19047-1749 © 2010 Insight Pharmaceuticals Corporation

Questions?

Call 1-888-542-3546
www.prontoplus.com

PRINCIPAL DISPLAY PANEL - 59 mL Carton

FULL PRESCRIPTION STRENGTH

PRONTO®
PLUS

Pyrantel Pamoate Suspension

Pinworm Treatment

Doctor Recommended Ingredient

- Eliminates Pinworms with One Dose
- Relieves Itching and Irritation
  from Pinworms
- Child Resistant Cap

Great Cherry Taste
Sugar Free

2 FL OZ (59 mL)

NEW FAMILY SIZE

Do not use if foil seal under bottle cap imprinted with
"Sealed for Your Protection" is broken or missing.